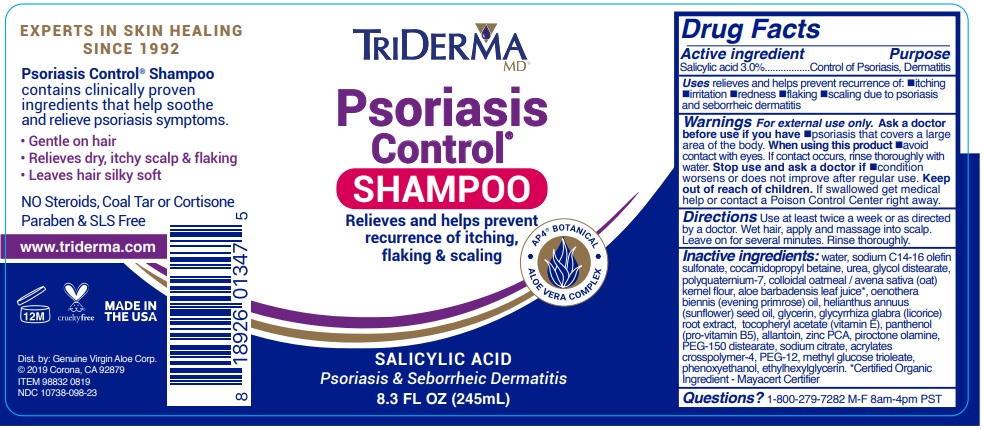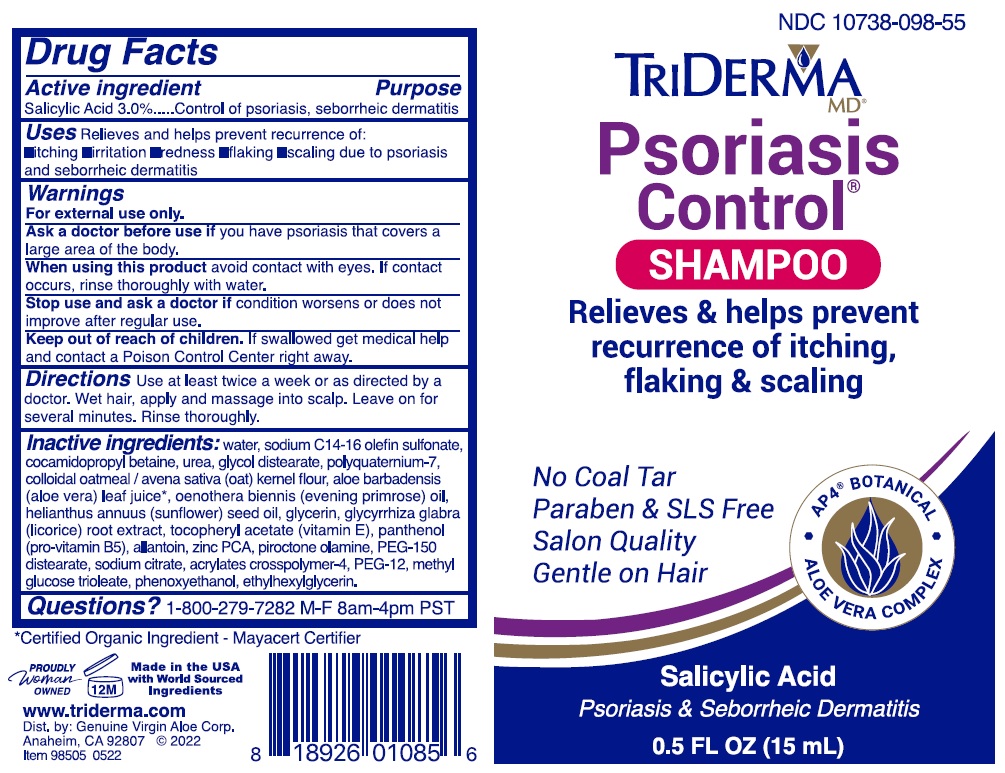 DRUG LABEL: PSORIASIS CONTROL
NDC: 10738-098 | Form: GEL
Manufacturer: Genuine Virgin Aloe Corporation
Category: otc | Type: HUMAN OTC DRUG LABEL
Date: 20220513

ACTIVE INGREDIENTS: SALICYLIC ACID 3 g/100 mL
INACTIVE INGREDIENTS: WATER; SODIUM C14-16 OLEFIN SULFONATE; COCAMIDOPROPYL BETAINE; (1,1-DIMETHYLETHYL)UREA; GLYCOL DISTEARATE; POLYQUATERNIUM-7 (70/30 ACRYLAMIDE/DADMAC; 1600000 MW); OATMEAL; ALOE VERA LEAF; EVENING PRIMROSE OIL; SUNFLOWER OIL; GLYCERIN; GLYCYRRHIZA GLABRA; .ALPHA.-TOCOPHEROL ACETATE, DL-; PANTHENOL; ALLANTOIN; ZINC PIDOLATE; PIROCTONE OLAMINE; PEG-150 DISTEARATE; SODIUM CITRATE, UNSPECIFIED FORM; BUTYL ACRYLATE/METHYL METHACRYLATE/METHACRYLIC ACID COPOLYMER (18000 MW); POLYETHYLENE GLYCOL 600; METHYL GLUCOSE DIOLEATE; PHENOXYETHANOL; ETHYLHEXYLGLYCERIN

TRIDERMA Psoriasis Control SHAMPOO

Active ingredient

Salicylic acid 3.0%

Purpose

Control of Psoriasis, Dermatitis

INDICATIONS AND USAGE

Uses relieves and helps prevent recurrence of: •itching •irritation •redness •flaking •scaling due to psoriasis and seborrheic dermatitis

WARNINGS

Warnings For external use only. Ask a doctor before use if you have •psoriasis that covers a large area of the body. When using this product •avoid contact with eyes. If contact occurs, rinse thoroughly with water. Stop use and ask a doctor if •condition worsens or does not improve after regular use.

Keep out of reach of children. If swallowed get medical help or contact a Poison Control Center right away.

DOSAGE AND ADMINISTRATION

Directions Use at least twice a week or as directed by a doctor. Wet hair, apply and massage into scalp.
Leave on for several minutes. Rinse thoroughly.

INACTIVE INGREDIENT

Inactive ingredients: water, sodium C14-16 olefin sulfonate, cocamidopropyl betaine, urea, glycol distearate, polyquaternium-7, colloidal oatmeal / avena sativa (oat) kernel flour, aloe barbadensis leaf juice*, oenothera biennis (evening primrose) oil, helianthus annuus (sunflower) seed oil, glycerin, glycyrrhiza glabra (licorice) root extract, tocopheryl acetate (vitamin E), panthenol (pro-vitamin B5), allantoin, zinc PCA, piroctone olamine, PEG-150 distearate, sodium citrate, acrylates crosspolymer-4, PEG-12, methyl glucose trioleate, phenoxyethanol, ethylhexylglycerin. *Certified Organic Ingredient - Mayacert Certifier

QUESTIONS

Questions? 1-800-279-7282 M-F 8am-4pm PST

Relieves and helps prevent recurrence of itching, flaking & scaling

AP4 BOTANICAL

ALOE VERA COMPLEX

SALICYLIC ACID

Psoriasis & Seborrheic Dermatitis

EXPERTS IN SKIN HEALING SINCE 1992

Psoriasis Control® Shampoo contains clinically proven ingredients that help soothe and relieve psoriasis symptoms.

• Gentle on hair
• Relieves dry, itchy scalp & flaking
• Leaves hair silky soft

NO Steroids, Coal Tar or Cortisone Paraben & SLS Free

www.triderma.com

MADE IN THE USA

Dist. by: Genuine Virgin Aloe Corp.

Corona, CA 92879

Packaging

0.5 oz tube